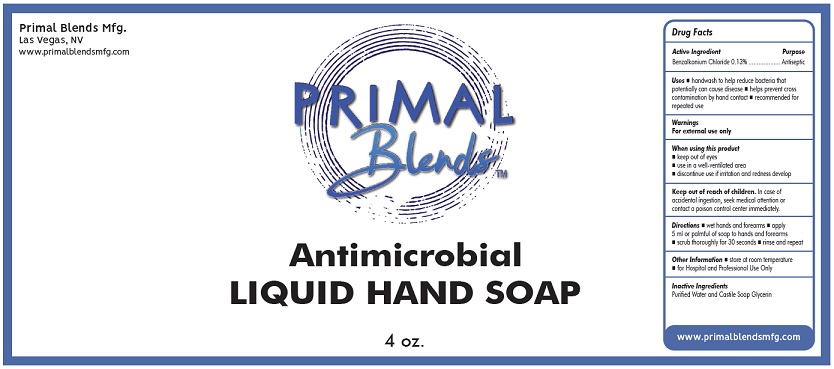 DRUG LABEL: Primal Blends
NDC: 75494-005 | Form: LIQUID
Manufacturer: Alchemy Nutra LLC
Category: otc | Type: HUMAN OTC DRUG LABEL
Date: 20200519

ACTIVE INGREDIENTS: BENZALKONIUM CHLORIDE 1.3 g/1000 mL
INACTIVE INGREDIENTS: GLYCERIN; WATER; COCONUT OIL; SUNFLOWER OIL; ROSEMARY

Active Ingredient

Benzalkonium Chloride 0.13%

Purpose

Antiseptic

Uses

- handwash to help reduce bacteria that potentially can cause disease
- helps prevent cross contamination by hand contact
- recommended for repeated use

Warnings

For external use only.

When using this product

- keep out of eyes
- use in a well-ventilated area
- discontinue use if irritation and redness develops

Keep out of reach of children. In case of accidental ingestion, seek medical attention or contact a poison control center immediately.

Directions

- wet hands and forearms
- apply 5 ml or palmful of soap to hands and forearms
- scrub thoroughly for 30 seconds
- rinse and repeat

Other Information

- store at room temperature
- for Hospital and Professional Use Only

Inactive ingredients

Purified Water and Castile Soap Glycerin